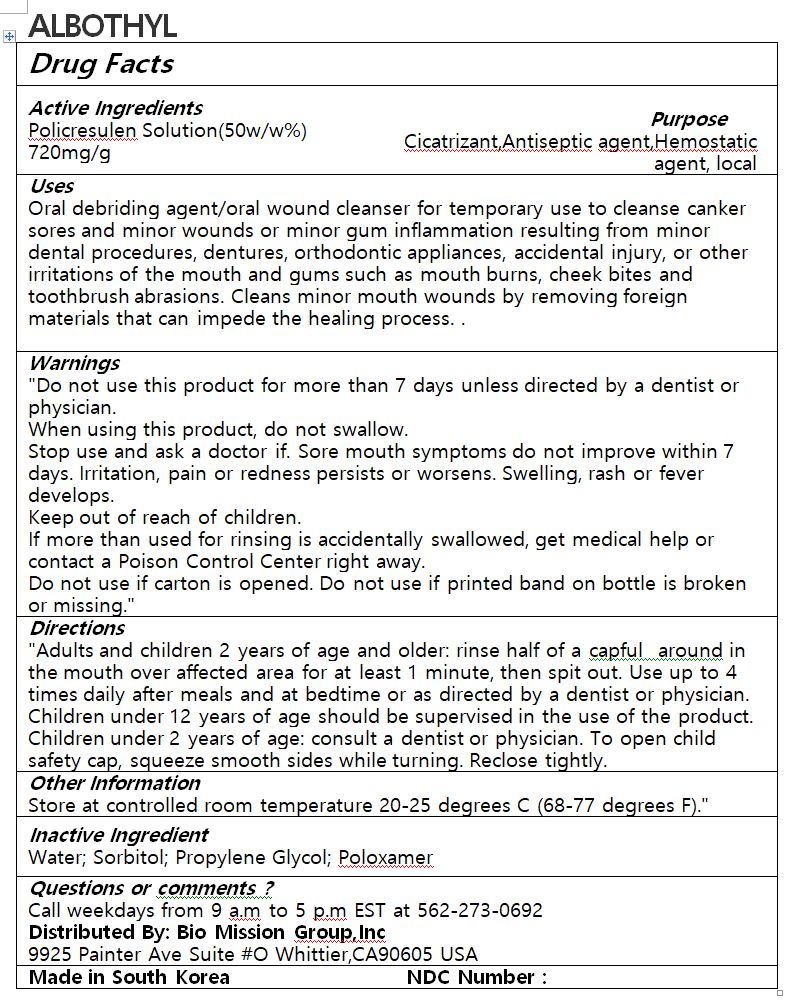 DRUG LABEL: ALBOTHYL
NDC: 72988-0035 | Form: LIQUID
Manufacturer: Lydia Co., Ltd.
Category: otc | Type: HUMAN OTC DRUG LABEL
Date: 20230710

ACTIVE INGREDIENTS: POLICRESULEN 720 mg/1 g
INACTIVE INGREDIENTS: WATER

ACTIVE INGREDIENT

Policresulen Solution

PURPOSE

Oral debriding agent/oral wound cleanser for temporary use to cleanse canker sores and minor wounds or minor gum inflammation resulting from minor dental procedures, dentures, orthodontic appliances, accidental injury, or other irritations of the mouth and gums such as mouth burns, cheek bites and toothbrush abrasions. Cleans minor mouth wounds by removing foreign materials that can impede the healing process

Keep out of reach of children

INDICATIONS AND USAGE

Adults and children 2 years of age and older: rinse half of a capful around in the mouth over affected area for at least 1 minute, then spit out. Use up to 4 times daily after meals and at bedtime or as directed by a dentist or physician. Children under 12 years of age should be supervised in the use of the product. Children under 2 years of age: consult a dentist or physician. To open child safety cap, squeeze smooth sides while turning. Reclose tightly

Do not use this product for more than 7 days unless directed by a dentist or physician.

When using this product, do not swallow.

Stop use and ask a doctor if. Sore mouth symptoms do not improve within 7 days. Irritation, pain or redness persists or worsens. Swelling, rash or fever develops.

Keep out of reach of children.

If more than used for rinsing is accidentally swallowed, get medical help or contact a Poison Control Center right away.

Do not use if carton is opened. Do not use if printed band on bottle is broken or missing

INACTIVE INGREDIENT

Water; Sorbitol; Propylene Glycol; Poloxamer

DOSAGE AND ADMINISTRATION

for oral use